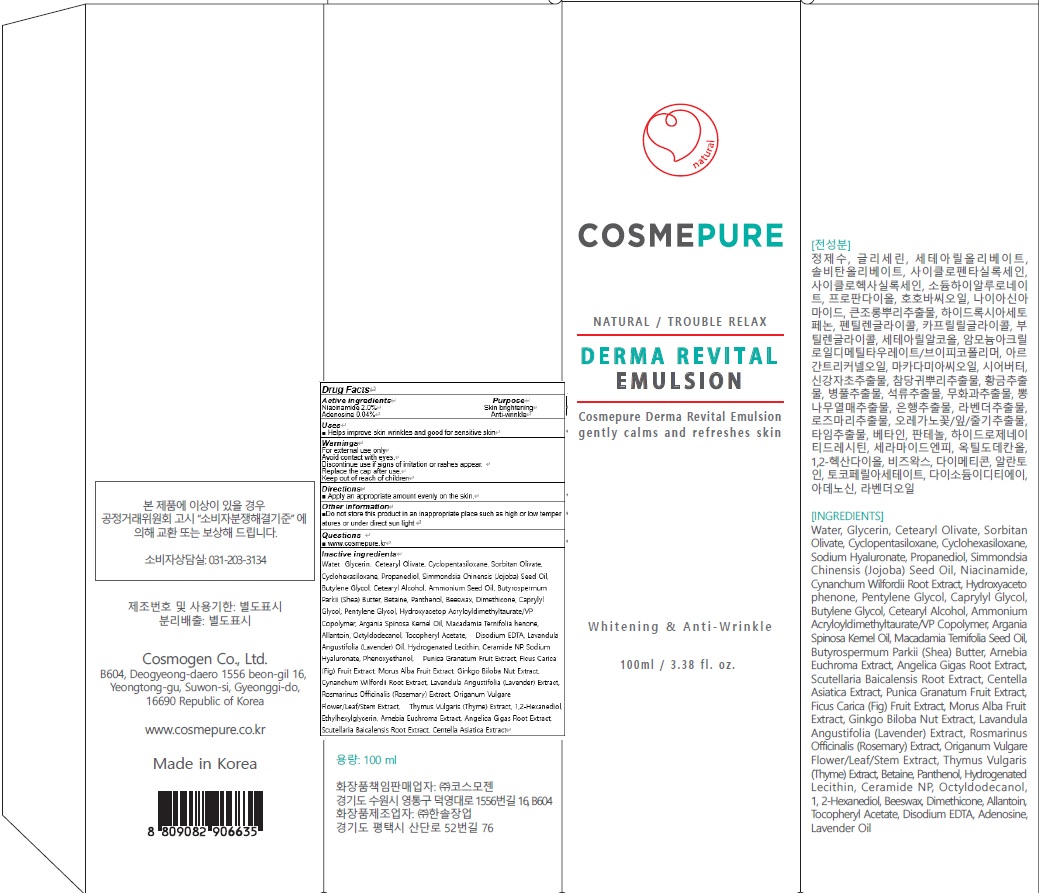 DRUG LABEL: COSMEPURE DERMA REVITAL
NDC: 81418-020 | Form: EMULSION
Manufacturer: Cosmogen Co., Ltd.
Category: otc | Type: HUMAN OTC DRUG LABEL
Date: 20210129

ACTIVE INGREDIENTS: Niacinamide 2.0 g/100 mL; Adenosine 0.04 g/100 mL
INACTIVE INGREDIENTS: Water; Glycerin

ACTIVE INGREDIENTS

Niacinamide 2.0%
Adenosine 0.04%

INACTIVE INGREDIENTS

Water, Glycerin, Cetearyl Olivate, Cyclopentasiloxane, Sorbitan Olivate, Cyclohexasiloxane, Propanediol, Simmondsia Chinensis (Jojoba) Seed Oil, Butylene Glycol, Cetearyl Alcohol, Ammonium Seed Oil, Butyrospermum Parkii (Shea) Butter, Betaine, Panthenol, Beeswax, Dimethicone, Caprylyl Glycol, Pentylene Glycol, Hydroxyacetop Acryloyldimethyltaurate/VP Copolymer, Argania Spinosa Kernel Oil, Macadamia Ternifolia henone, Allantoin, Octyldodecanol, Tocopheryl Acetate, Disodium EDTA, Lavandula Angustifolia (Lavender) Oil, Hydrogenated Lecithin, Ceramide NP, Sodium Hyaluronate, Phenoxyethanol, Punica Granatum Fruit Extract, Ficus Carica (Fig) Fruit Extract, Morus Alba Fruit Extract, Ginkgo Biloba Nut Extract, Cynanchum Wilfordii Root Extract, Lavandula Angustifolia (Lavender) Extract, Rosmarinus Officinalis (Rosemary) Extract, Origanum Vulgare Flower/Leaf/Stem Extract, Thymus Vulgaris (Thyme) Extract, 1,2-Hexanediol, Ethylhexylglycerin, Arnebia Euchroma Extract, Angelica Gigas Root Extract, Scutellaria Baicalensis Root Extract, Centella Asiatica Extract

PURPOSE

Skin brightening
Anti wrinkle

WARNINGS

For external use only
Avoid contact with eyes.
Discontinue use if signs of irritation or rashes appear.
Replace the cap after use.
Keep out of reach of children

KEEP OUT OF REACH OF CHILDREN

Uses

■ Helps improve skin wrinkles and good for sensitive skin

Directions

■ Apply an appropriate amount evenly on the skin.

Other information

■ Do not store this product in an inappropriate place such as high or low temperatures or under direct sun light

QUESTIONS

■ www.cosmepure.kr